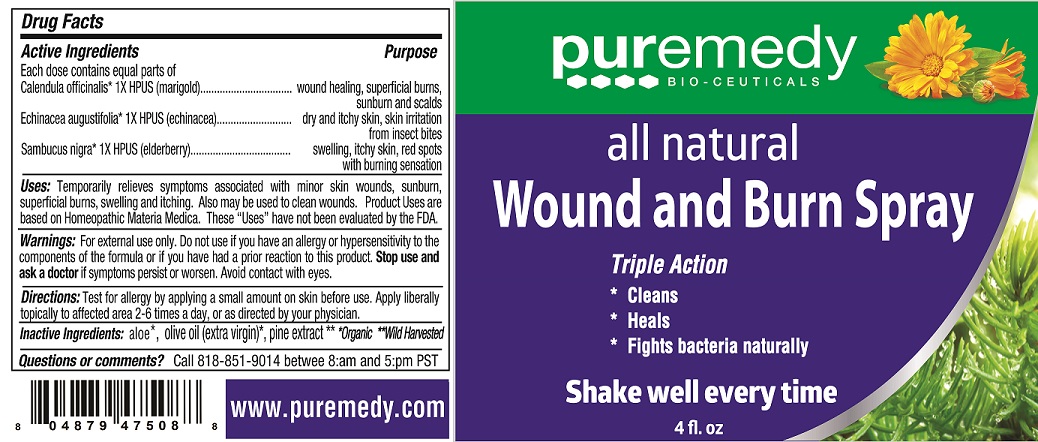 DRUG LABEL: ALL NATURAL WOUND AND BURN
NDC: 52810-219 | Form: SPRAY
Manufacturer: PUREMEDY
Category: homeopathic | Type: HUMAN OTC DRUG LABEL
Date: 20240111

ACTIVE INGREDIENTS: CALENDULA OFFICINALIS FLOWER 1 [hp_X]/100 mL; ECHINACEA ANGUSTIFOLIA 1 [hp_X]/100 mL; SAMBUCUS NIGRA FLOWER 1 [hp_X]/100 mL
INACTIVE INGREDIENTS: ALOE; OLIVE OIL; MARITIME PINE

ALL NATURAL WOUND AND BURN SPRAY (52810-219)

ACTIVE INGREDIENTS

CALENDULA OFFICINALIS (1X) HPUS (MARIGOLD)

ECHINACEA ANGUSTIFOLIA (1X) HPUS (ECHINACEA)

SAMBUCUS NIGRA (1X) HPUS (ELDERBERRY)

PURPOSE

SWELLING, ITCHY SKIN, RED SPOTS WITH BURNING SENSATION

WOUND HEALING, SUPERFICIAL BURNS, SUNBURN AND SCALDS

DRY AND ITCHY SKIN, SKIN IRRITATION FROM INSECT BITES

INDICATIONS AND USAGE

USES: TEMPORARITY RELIEVES SYMPTOMS ASSOCIATED WITH MINOR SKIN WOUNDS,

SUNBURN, SUPERFICIAL BURNS, SWELLING AND ITCHING. ALSO MAY BE USED TO CLEAN

WOUNDS. PRODUCT USES ARE BASED ON HOMEOPATHIC MATERIA MEDICA. THESE "USES"

HAVE NOT BEEN EVALUATED BY THE FDA.

DOSAGE AND ADMINISTRATION

DIRECTIONS: TEST FOR ALLERGY BY APPLYING A SMALL AMOUNT ON SKIN BEFORE USE.

APPLY TOPICALLY TO AFFECTED AREA 2-6 TIMES A DAY, OR AS DIRECTED BY YOUR PHYSICIAN.

INACTIVE INGREDIENT

INACTIVE INGREDIENTS: ORGANIC ALOE, ORGANIC OLIVE OIL (EXTRA VIRGIN), WILD HARVESTED PINE EXTRACT

WARNINGS

WARNING: FOR EXTERNAL USE ONLY. DO NOT USE IF YOU HAVE AN ALLERGY OR

HYPERSENSITIVITY TO THE COMPONENTS OF THE FORMULA OR IF YOU HAVE HAD

PRIOR REACTION TO THIS SALVE, STOP USE AND ASK A DOCTOR IF SYMPTOMS

PERSIST OR WORSEN. AVOID CONTACT WITH EYES.

KEEP OUT OF REACH OF CHILDREN.

QUESTIONS OR COMMENTS: CALL 818-851-9014 BETWEEN8:AM - 5:PM PST